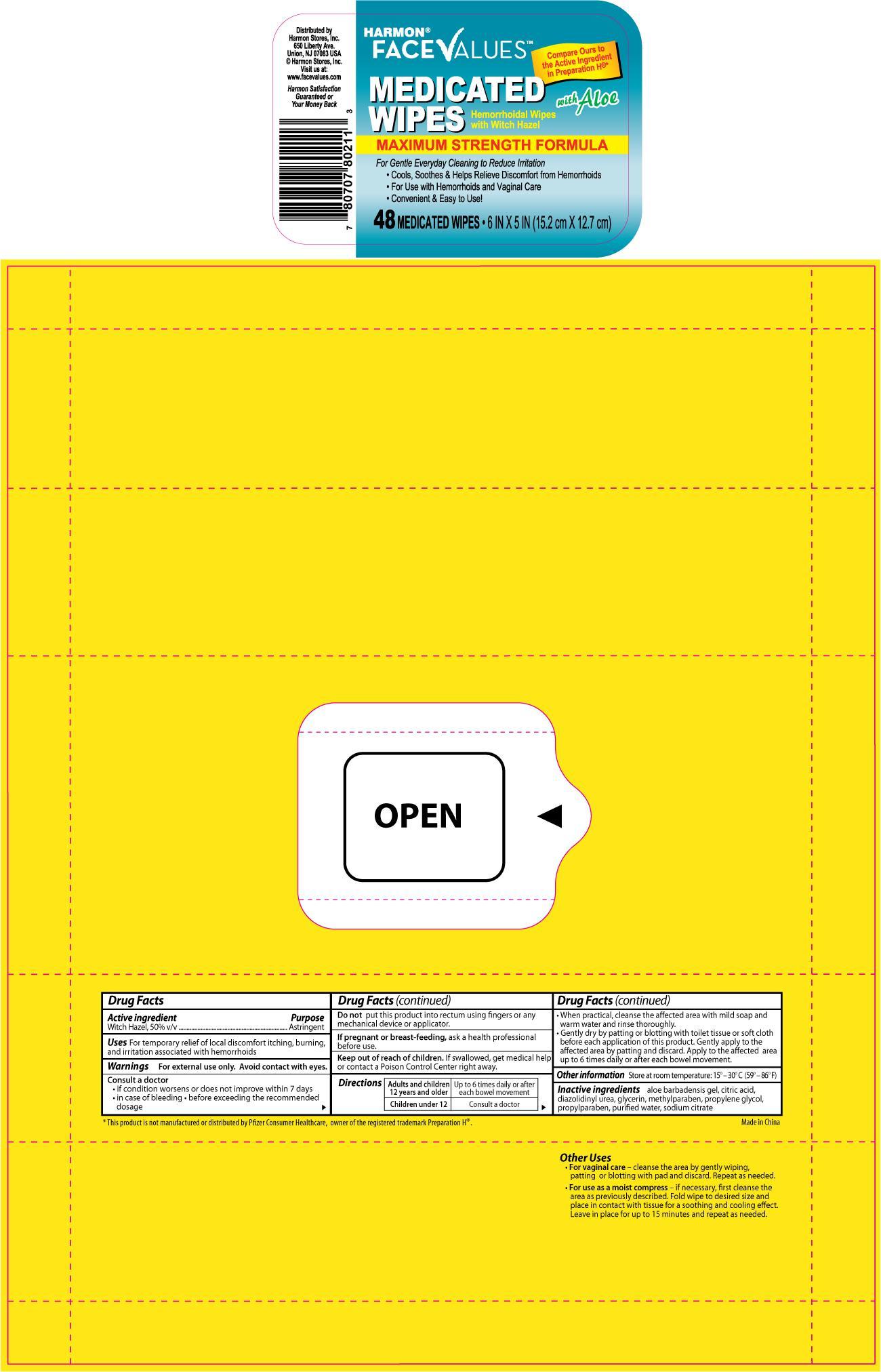 DRUG LABEL: HARMON FACE VALUES MEDICATED WIPES
                
NDC: 63940-802 | Form: CLOTH
Manufacturer: HARMON STORES INC.
Category: otc | Type: HUMAN OTC DRUG LABEL
Date: 20120731

ACTIVE INGREDIENTS: WITCH HAZEL 5 g/1 1
INACTIVE INGREDIENTS: CITRIC ACID MONOHYDRATE; DIAZOLIDINYL UREA; GLYCERIN; METHYLPARABEN; PROPYLENE GLYCOL; PROPYLPARABEN; WATER

Drug Facts

Active ingredient Purpose

Witch Hazel, 50% v/v...........................................................Astringent

Uses

For temporary relief of local discomfort itching, burning, and irritation associated with hermorrhoids

Warnings

For external use only. Avoid contact with eyes.

Consult a doctor

- if condition worsens or does not improve within 7 days
- in case of bleeding
- before exceeding the recommended dosage

DO NOT USE

Do not put this product into rectum using fingers or any mechanical device or applicator.

PREGNANCY OR BREAST FEEDING

If pregnant or breast-feeding, ask a health professional before use.

Keep out of reach of children.

If swallowed, get medical help or contact a Poison Control Center right away.

Directions

Adults and children 12 years and older- Up to 6 times daily or after each bowel movement

Children under 12- Consult a doctor

When practical, cleanse the affected area with mild soap and warm water and rinse thoroughly.

Gently dry by patting or blotting with toilet tissue or soft cloth before each application of this product.

Gently apply to the affected area by patting and discard. Apply to the affected area up to 6 times daily or after each bowel movement.

STORAGE AND HANDLING

Store at room temperature: 15o-30oC (59o-86oF)

Inactive ingredients

aloe barbadensis gel, citric acid, diazolidinyl urea, glycerin, methylparaben, propylene glycol, propylparaben, purified water, sodium citrate

DOSAGE AND ADMINISTRATION

Distributed by

Harmon Stores Inc.

550 Liberty Ave.

Union, NJ 07083

Visit us at www.facevalue.com

Made in China

PACKAGE LABEL

Enter section text here